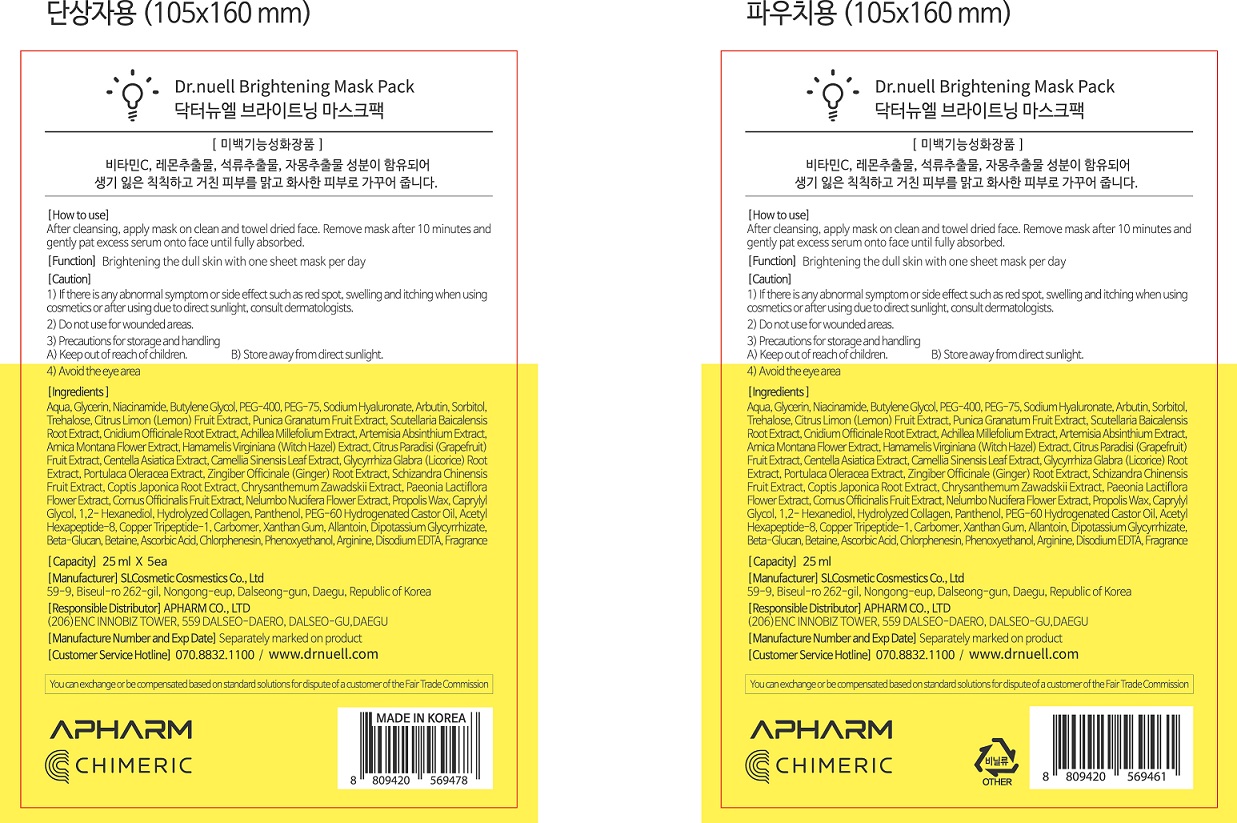 DRUG LABEL: Dr.NUELL Brightening Mask Pack
NDC: 73430-0001 | Form: LIQUID
Manufacturer: Apharm Co., Ltd.
Category: otc | Type: HUMAN OTC DRUG LABEL
Date: 20191102

ACTIVE INGREDIENTS: GLYCERIN 10 g/100 mL
INACTIVE INGREDIENTS: ARBUTIN; BUTYLENE GLYCOL

ACTIVE INGREDIENT

glycerin

PURPOSE

Brightening the dull skin with one sheet mask per day

Keep out of reach of children

INDICATIONS AND USAGE

After cleansing, apply mask on clean and towel dried face.

Remove mask after 10 minutes and gently pat excess serum onto face until fully absorbed

WARNINGS

1) if there is any abnormal symptom or side effect, such as red spot, swelling and itching when using cosmetlcs or after using due to direct sunlight, consult dermatologists
2) Do not use for wounded areas
3) Precautions for storage and handling
keep out of reach of children, store away from direct sunlight
4) avoid the eye area

INACTIVE INGREDIENT

water, peg-400, sodium hyaluronate, etc.

DOSAGE AND ADMINISTRATION

For external use only